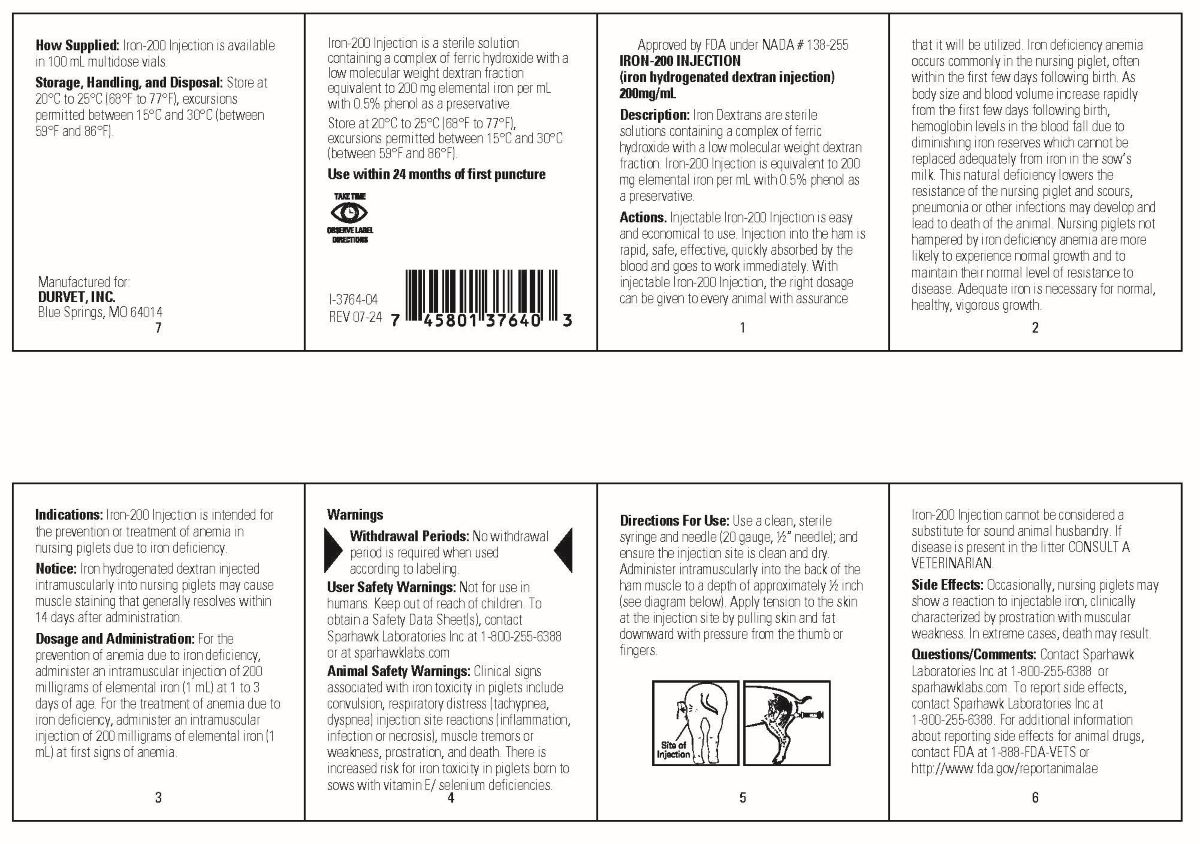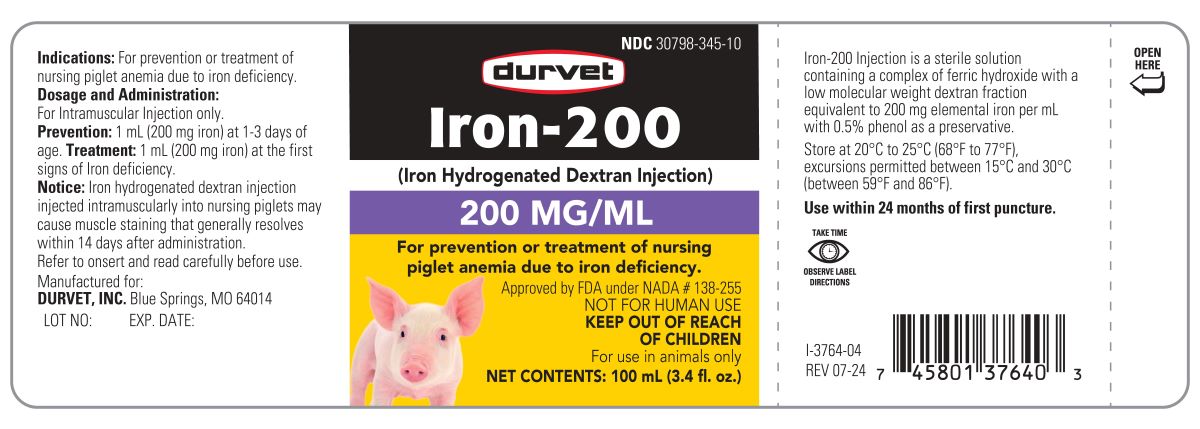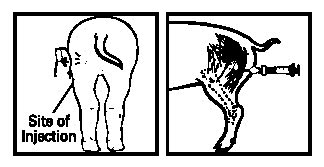 DRUG LABEL: IRON
NDC: 30798-345 | Form: INJECTION
Manufacturer: Durvet, Inc.
Category: animal | Type: OTC ANIMAL DRUG LABEL
Date: 20241202

ACTIVE INGREDIENTS: IRON 200 mg/1 mL
INACTIVE INGREDIENTS: PHENOL .5 mg/1 mL

IRON-200 (Iron Hydrogenated Dextran Injection)

INDICATIONS AND USAGE

Iron-200
For prevention or treatment of nursing
piglet anemia due to iron deficiency.
Approved by FDA under NADA # 138-255
NOT FOR HUMAN USE
KEEP OUT OF REACH OF CHILDREN
For use in animals only

Indications: For prevention or treatment of nursing piglet anemia due to iron deficiency.
Dosage and Administration:
For Intramuscular Injection only.
Prevention: 1 mL (200 mg iron) at 1-3 days of
age. Treatment: 1 mL (200 mg iron) at the first
signs of Iron deficiency.
Notice: Iron hydrogenated dextran injection
injected intramuscularly into nursing piglets may
cause muscle staining that generally resolves
within 14 days after administration.
Refer to onsert and read carefully before use.

Iron-200 Injection is a sterile solution
containing a complex of ferric hydroxide with a low molecular weight dextran fraction equivalent to
200 mg elemental iron per mL with 0.5% phenol as a preservative.
Store at 20°C to 25°C (68°F to 77°F), excursions permitted between 15°C and 30°C (between 59°F and
86°F).
Use within 24 months of first puncture.

DESCRIPTION

Approved by FDA under NADA # 138-255

IRON-200 INJECTION
(iron hydrogenated dextran injection)

200mg/mL
Description: Iron Dextrans are sterile solutions containing a complex of ferric hydroxide with a low molecular weight dextran fraction. Iron-200 Injection is equivalent to 200 mg elemental iron per mL with 0.5% phenol as a preservative.

Actions. Injectable Iron-200 Injection is easy and economical to use. Injection into the ham is rapid, safe, effective, quickly absorbed by the blood and goes to work immediately. With injectable Iron-200 Injection, the right dosage can be given to every animal with assurance that it will be utilized. Iron deficiency anemia occurs commonly in the nursing piglet, often within the first few days following birth. As body size and blood volume increase rapidly from the first few days following birth, hemoglobin levels in the blood fall due to diminishing iron reserves which cannot be replaced adequately from iron in the sow’s milk. This natural deficiency lowers the resistance of the nursing piglet and scours, pneumonia or other infections may develop and lead to death of the animal. Nursing piglets not hampered by iron deficiency anemia are more likely to experience normal growth and to maintain their normal level of resistance to disease. Adequate iron is necessary for normal, healthy, vigorous growth.

INDICATIONS AND USAGE

Indications: Iron-200 Injection is intended for the prevention or treatment of anemia in nursing piglets due to iron deficiency.
Notice: Iron hydrogenated dextran injected intramuscularly into nursing piglets may cause muscle staining that generally resolves within 14 days after administration.
Dosage and Administration: For the prevention of anemia due to iron deficiency, administer an intramuscular injection of 200 milligrams of elemental iron (1 mL) at 1 to 3 days of age. For the treatment of anemia due to iron deficiency, administer an intramuscular injection of 200 milligrams of elemental iron (1 mL) at first signs of anemia.

Warnings

Withdrawal Periods: No withdrawal period is required when used according to labeling.

User Safety Warnings: Not for use in humans. Keep out of reach of children. To obtain a Safety Data Sheet(s), contact Sparhawk Laboratories Inc at 1-800-255-6388 or at sparhawklabs.com
Animal Safety Warnings: Clinical signs associated with iron toxicity in piglets include convulsion, respiratory distress (tachypnea, dyspnea) injection site reactions (inflammation, infection or necrosis), muscle tremors or weakness, prostration, and death. There is increased risk for iron toxicity in piglets born to sows with vitamin E/ selenium deficiencies.

DOSAGE AND ADMINISTRATION

Directions For Use: Use a clean, sterile syringe and needle (20 gauge, ½” needle); and ensure the injection site is clean and dry. Administer intramuscularly into the back of the ham muscle to a depth of approximately ½ inch (see diagram below). Apply tension to the skin at the injection site by pulling skin and fat downward with pressure from the thumb or fingers.

Iron-200 Injection cannot be considered a substitute for sound animal husbandry. If disease is present in the litter CONSULT A VETERINARIAN.

Side Effects: Occasionally, nursing piglets may show a reaction to injectable iron, clinically characterized by prostration with muscular weakness. In extreme cases, death may result.

Questions/Comments: Contact Sparhawk Laboratories Inc at 1-800-255-6388 or sparhawklabs.com. To report side effects, contact Sparhawk Laboratories Inc at 1-800-255-6388. For additional information about reporting side effects for animal drugs, contact FDA at 1-888-FDA-VETS or
http://www.fda.gov/reportanimalae

HOW SUPPLIED

How Supplied: Iron-200 Injection is available in 100 mL multidose vials.

STORAGE AND HANDLING

Storage, Handling, and Disposal: Store at 20°C to 25°C (68°F to 77°F), excursions permitted between 15°C and 30°C (between 59°F and 86°F).